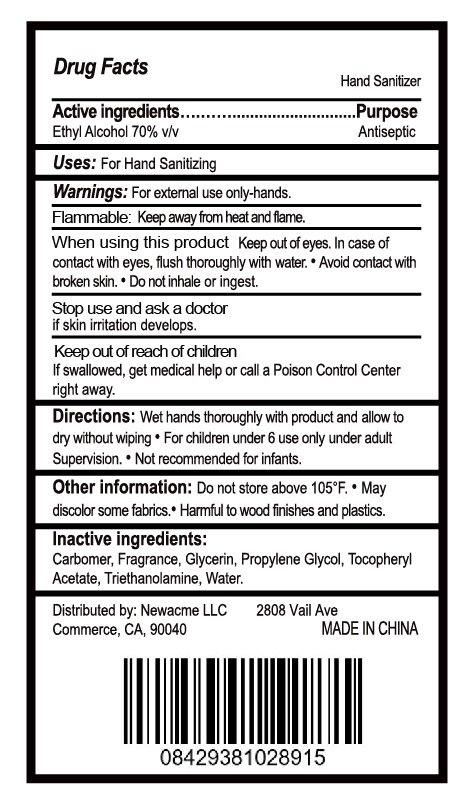 DRUG LABEL: Hand Sanitizer
NDC: 77753-004 | Form: GEL
Manufacturer: SHANDISHI Biological Technology Co., Ltd.
Category: otc | Type: HUMAN OTC DRUG LABEL
Date: 20200609

ACTIVE INGREDIENTS: ALCOHOL 70 mL/100 mL
INACTIVE INGREDIENTS: WATER; ALPHA-TOCOPHEROL ACETATE; CARBOXYPOLYMETHYLENE; PROPYLENE GLYCOL; GLYCERIN; TROLAMINE

77753-004 Hand Sanitizer 70% Alcohol

Active ingredient

Ethyl Alcohol 70% v/v

Purpose

Antiseptic

Uses

For Hand Sanitizing

Warnings

Warnings: For external use only-hands.
Flammable: Keep away from heat and flame.
When using this product Keep out of eyes. In case of
contact with eyes, flush thoroughly with water.●Avoid contact with
broken skin.●Do not inhale or ingest.
Stop use and ask a doctor
if skin irritation develops.

Keep out of reach of children.

If swallowed, get medical help or call a Poison Control Center right away.

Directions

Wet hands thoroughly with product and allow to
dry without wiping●For children under 6 use only under adult
Supervision.●Not recommended for infants.

Other information

1 Do not store above 105°F
1 May discolor some fabrics

Inactive ingredients

Carbomer, Fragrance, Glycerin, Propylene Glycol, Tocopheryl
Acetate, Triethanolamine, Water.